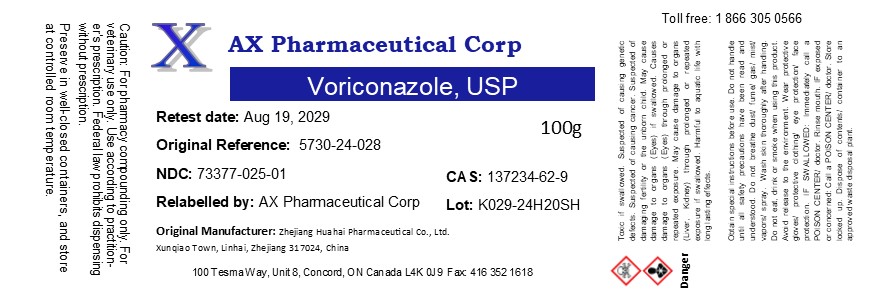 DRUG LABEL: Voriconazole
NDC: 73377-316 | Form: POWDER
Manufacturer: AX Pharmaceutical Corp
Category: other | Type: BULK INGREDIENT - ANIMAL DRUG
Date: 20250403

ACTIVE INGREDIENTS: Voriconazole 1 g/1 g

Voriconazole